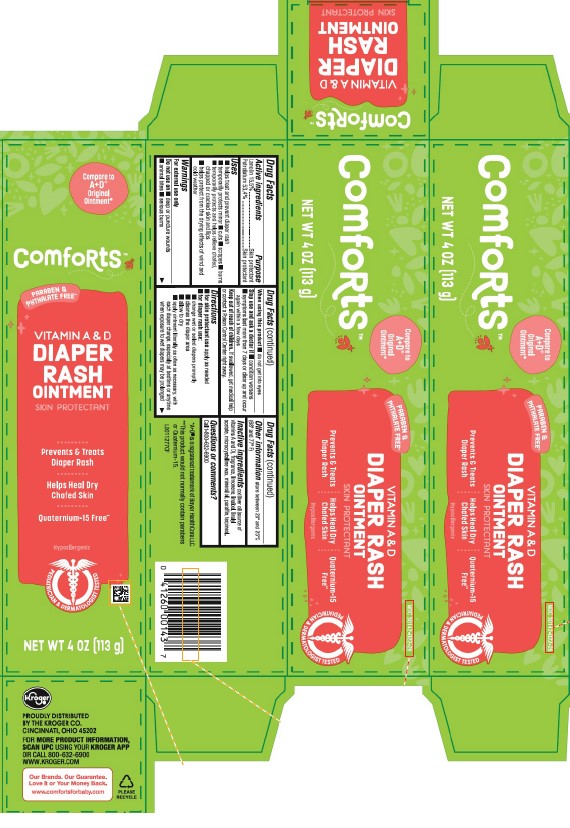 DRUG LABEL: Vitamin A D
NDC: 30142-022 | Form: OINTMENT
Manufacturer: Kroger Co.
Category: otc | Type: HUMAN OTC DRUG LABEL
Date: 20260202

ACTIVE INGREDIENTS: LANOLIN 155 mg/1 g; PETROLATUM 534 mg/1 g
INACTIVE INGREDIENTS: COD LIVER OIL; LIMONENE, (+)-; LINALOOL, (+/-)-; LINALYL ACETATE; MICROCRYSTALLINE WAX; MINERAL OIL; PARAFFIN; TERPINEOL

Comforts 013.001/013AC
Vitamin A & D Ointment

Active ingredients

Lanolin 15.5%

Petrolatum 53.4%

Purpose

Skin protectant

Uses

- helps treat and prevent diaper rash
- temporarily protects minor -cuts -scrapes -burns
- temporarily protects and helps relieve chafed, chapped or cracked skin and lips
- helps protect from the drying effects of wind and cold weather

Warnings

For external use only

Do not use on

- deep or puncture wounds
- animal bites
- serious burns

When using this product

- do not get into eyes

Stop use and ask a doctor if

- condition worsens
- symptoms last more than 7 days or clear up and occur again within a few days

Keep out of reach of children.

If swallowed, get medical help or contact a Poison Control Center right away.

Directions

- for skin protectant use apply as needed
- for diaper rash use:
- change wet or soiled diapers promptly
- cleanse the diaper area
- allow to dry
- apply ointment liberally as often as necessary, with each diaper change, especially at bedtime or anytime when exposure to wet diapers may be prolonged

Other information

store between 20º and 25ºC (68º and 77ºF)

Inactive ingredients

cod liver oil {(contains vitamins A & D)}, fragrance, limonene, linalool, linalyl acetate, microcrystalline wax, mineral oil, paraffin, terpineol

Questions or comments?

Call 1-800-632-6900

Disclaimer

*A+D®is a registered trademark of Bayer HealthCare LLC.

**This product would not normally contain parabens or Quaternium 15.

Adverse Reactions

Kroger®

PROUDLY DISTRIBUTED BY THE KROGER CO.

CINCINNATI, OH 45202

FOR MORE PRODUCT INFORMATION, SCAN UPC USING YOUR KROGER APP OR CALL 1-800-632-6900

WWW.KROGER.COM

Our Brands. Our Guarantee.

Love it or Your Money Back.

www.comfortsforbaby.com

Please Recycle

Principal display panel

NDC 30142-022-26

Comforts™

Compare to A+D® ORIGINAL OINTMENT*

PARABEN & PHTHALATE FREE**

VITAMIN A & D DIAPER RASH OINTMENT

SKIN PROTECTANT

Prevents & Treats Diaper Rash

Helps Heal Dry Chafed Skin

Quaternium-15 Free**

Hypoallergenic

PEDATRICIANS & DERMATOLOGIST TESTED

NET WT 4 OZ (113 g)